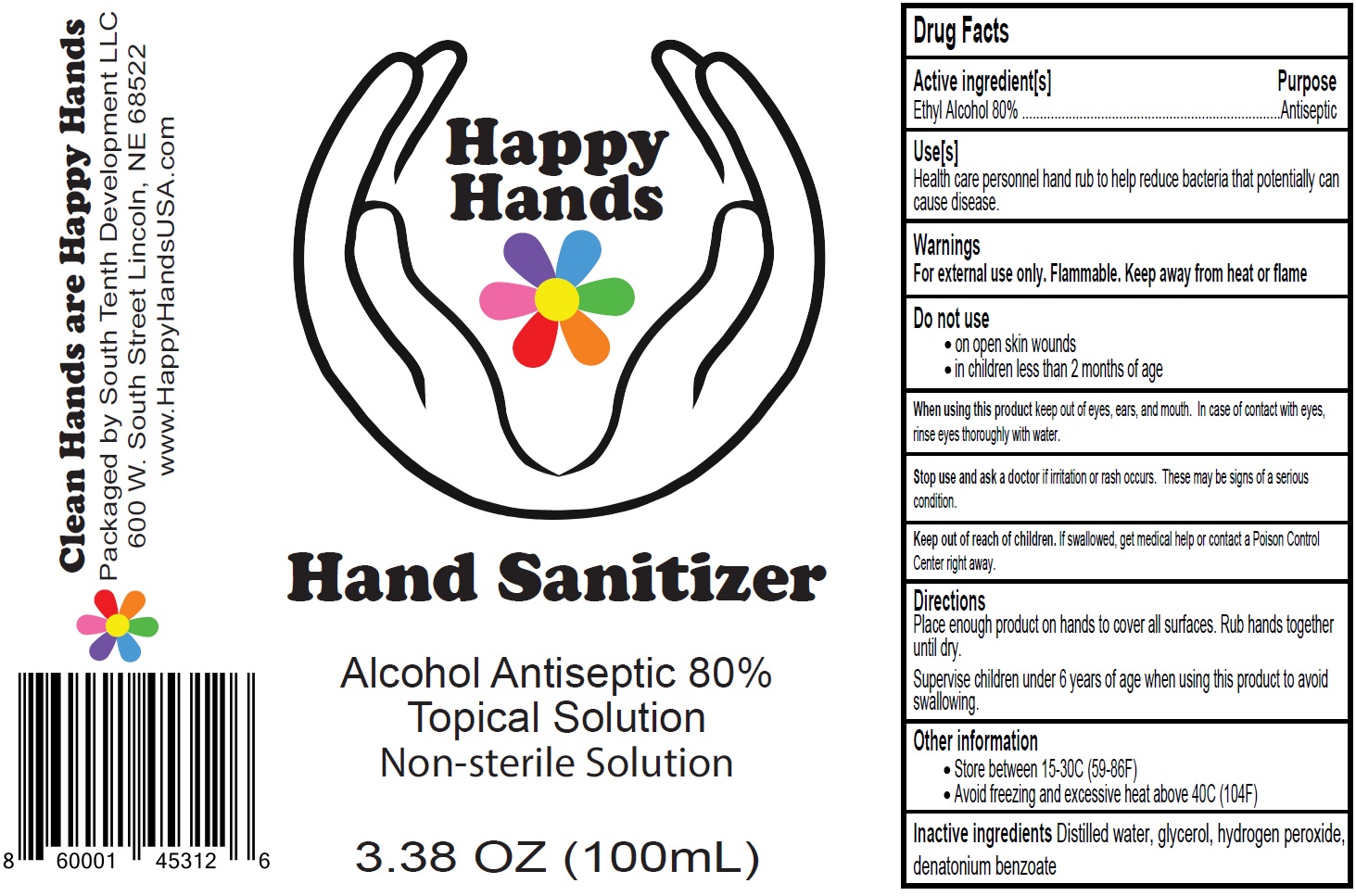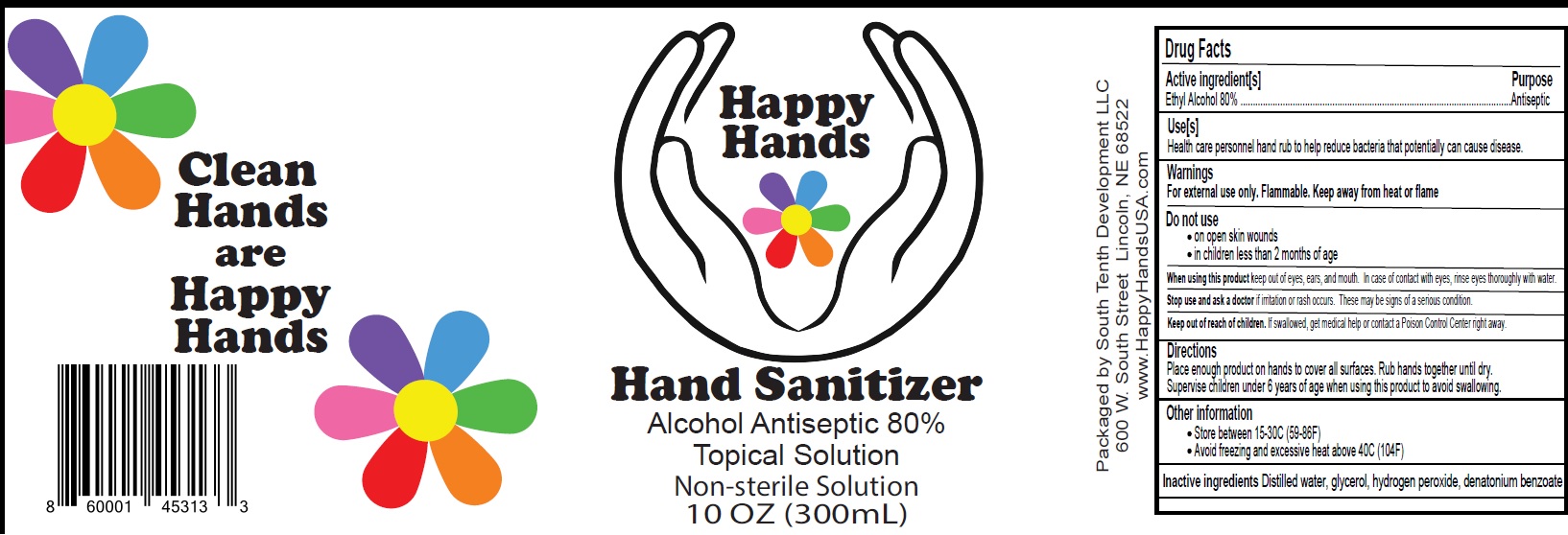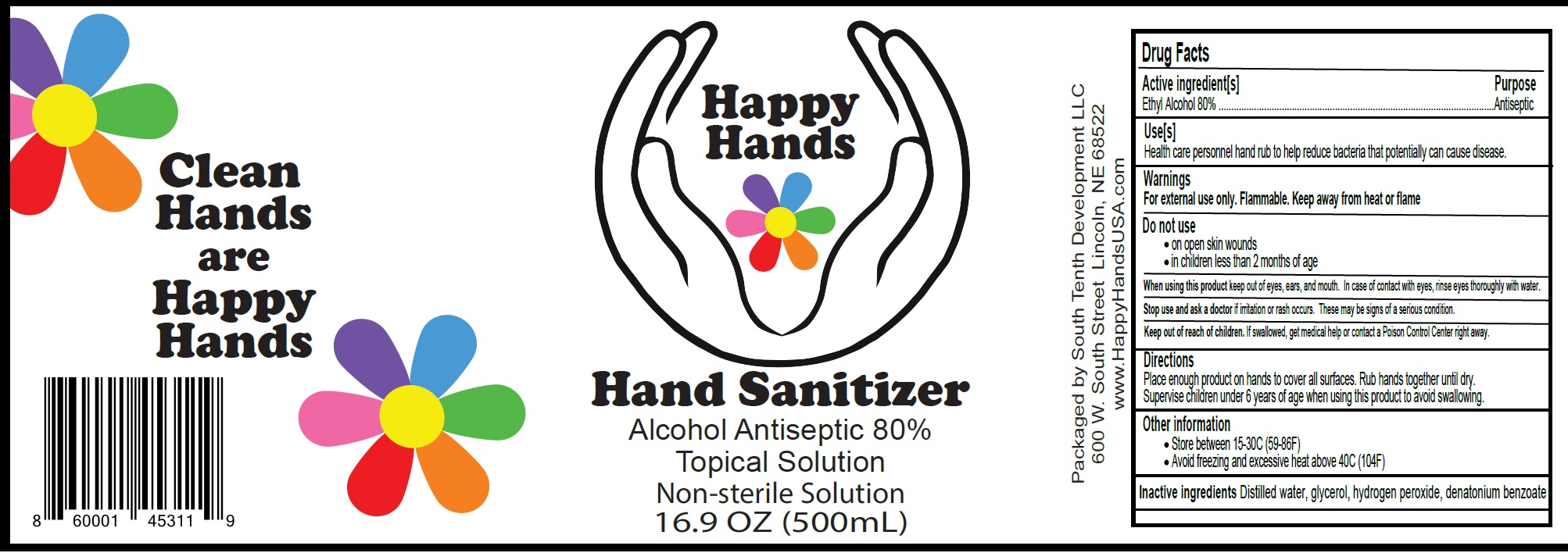 DRUG LABEL: Happy Hands Hand Sanitizer
NDC: 78705-001 | Form: LIQUID
Manufacturer: South Tenth Development, LLC
Category: otc | Type: HUMAN OTC DRUG LABEL
Date: 20200615

ACTIVE INGREDIENTS: ALCOHOL 0.8 mL/1 mL
INACTIVE INGREDIENTS: WATER; GLYCERIN; HYDROGEN PEROXIDE; DENATONIUM BENZOATE

"Happy Hands" Hand Sanitizer

Active Ingredient

Ethyl Alcohol 80%

Purpose

Antiseptic

Use[s]

Health care personnel hand rub to help reduce bacteria that potentially can cause disease.

Warnings

For external use only. Flammable. Keep away from heat or flame

Do not use

- on open skin wounds
- in children less than 2 months of age

When using this product

keep out of eyes, ears, and mouth. In case of contact with eyes, rinse eyes thoroughly with water.

Stop use & ask a doctor

if irritation or rash occurs. These may be signs of a serious condition.

Keep out of reach of children.

If swallowed, get medical help or contact a Poison Control Center right away.

Directions

Place enough product on hands to cover all surfaces. Rub hands together until dry.
Supervise children under 6 years of age when using this product to avoid swallowing.

Other Information

- Store between 15-30C (59-86F)
- Avoid freezing and excessive heat above 40C (104F)

Inactive Ingredients

Distilled water, glycerol, hydrogen peroxide, denatonium benzoate.